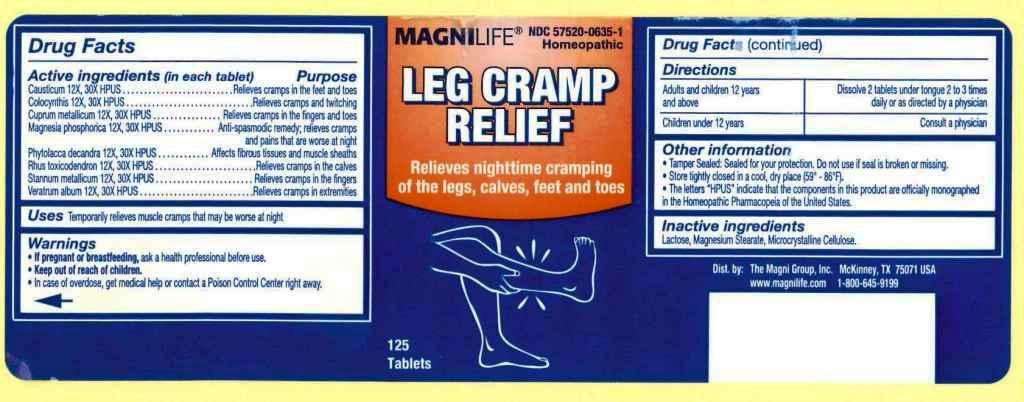 DRUG LABEL: Leg Cramp Relief
NDC: 57520-0635 | Form: TABLET
Manufacturer: Apotheca Company
Category: homeopathic | Type: HUMAN OTC DRUG LABEL
Date: 20110606

ACTIVE INGREDIENTS: CAUSTICUM 30 [hp_X]/1 1; CITRULLUS COLOCYNTHIS FRUIT PULP 30 [hp_X]/1 1; COPPER 30 [hp_X]/1 1; MAGNESIUM PHOSPHATE, DIBASIC TRIHYDRATE 30 [hp_X]/1 1; PHYTOLACCA AMERICANA ROOT 30 [hp_X]/1 1; TOXICODENDRON PUBESCENS LEAF 30 [hp_X]/1 1; TIN 30 [hp_X]/1 1; VERATRUM ALBUM ROOT 30 [hp_X]/1 1
INACTIVE INGREDIENTS: LACTOSE; MAGNESIUM STEARATE; CELLULOSE, MICROCRYSTALLINE

Leg Cramp Relief

ACTIVE INGREDIENT

ACTIVE INGREDIENTS: Causticum 12X, 30X, Colocynthis 12X, 30X, Cuprum metallicum 12X, 30X, Magnesia phosphorica 12X, 30X, Phytolacca decandra 12X, 30X, Rhus toxicodendron 12X, 30X, Stannum metallicum 12X, 30X, Veratrum album 12X, 30X.

PURPOSE

USES: Temporarily relieves muscle cramps that may be worse at night.

WARNINGS

WARNINGS: If pregnant or breastfeeding, ask a health professional before use.

Keep out of reach of children. In case of overdose, get medical help or contact a Poison Control Center right away.

OTHER INFORMATION: Tamper sealed: Sealed for your protection. Do not use if seal is broken or missing.

Store tightly closed in a cool, dry place (59-86 F).

The letters "HPUS" indicate that the components in this product are officially monographed in the Homeopathic Pharmacopeia of the United States.

DOSAGE AND ADMINISTRATION

DIRECTIONS: Adults and children 12 years and above: Dissolve 2 tablets under tongue 2 to 3 times daily or as directed by a physician.

Children under 12 years: Consult a physician.

INACTIVE INGREDIENT

INACTIVE INGREDIENTS: Lactose, Magnesium stearate, Microcrystalline cellulose.

KEEP OUT OF REACH OF CHILDREN. In case of overdose, get medical help or contact a Poison Control Center right away.

INDICATIONS AND USAGE

USES: Temporarily relieves muscle cramps that may be worse at night.

QUESTIONS

Dist. by:

The Magni Group, Inc.

McKinney, TX 75071 USA

www.magnilife.com

1-800-645-9199

PACKAGE LABEL

MAGNILIFE

NDC 57520-0635-1

Homeopathic

LEG CRAMP RELIEF

Relieves nighttime cramping of the legs, calves, feet and toes

125 Tablets